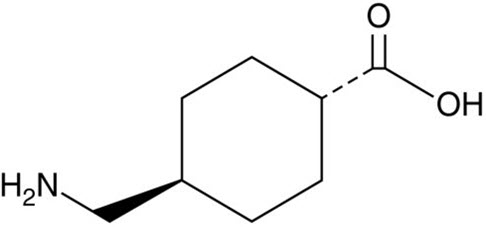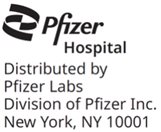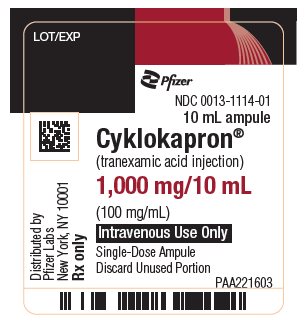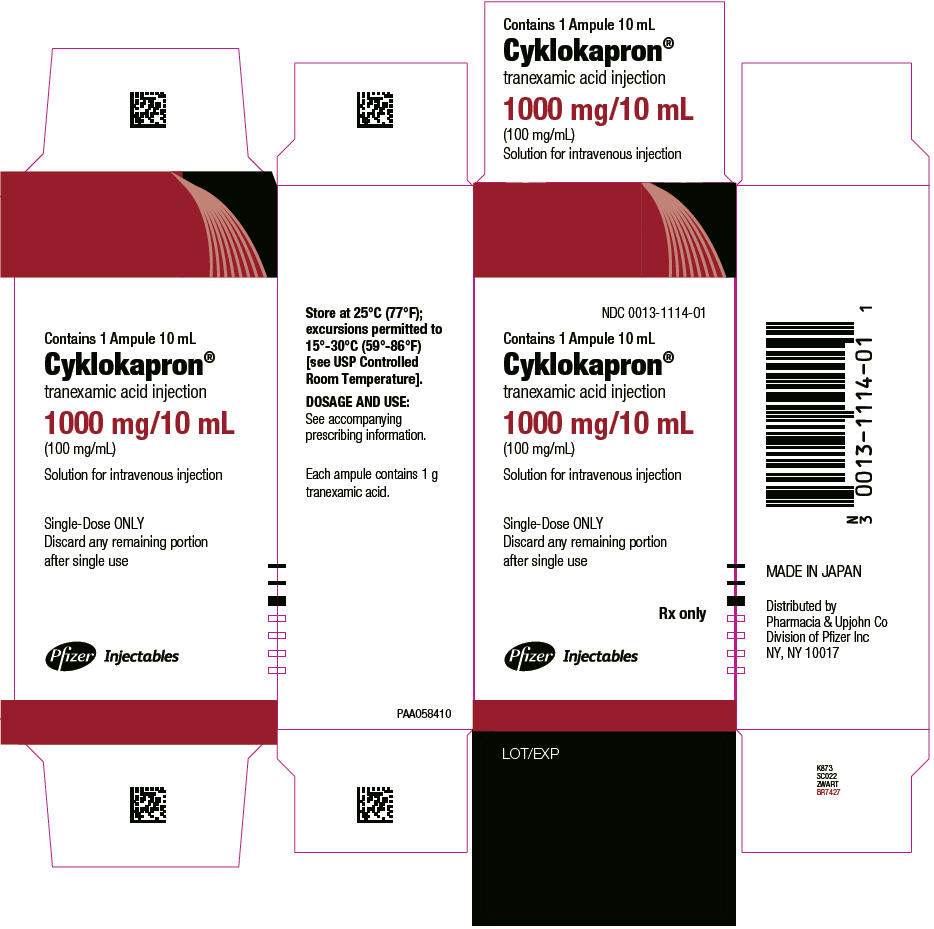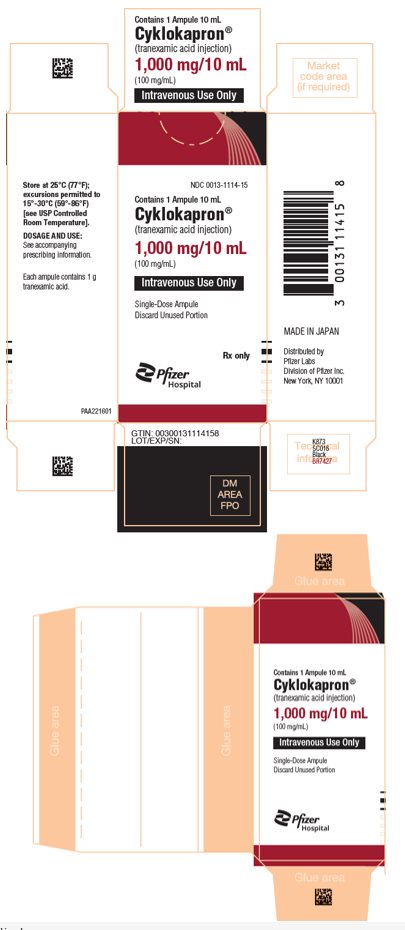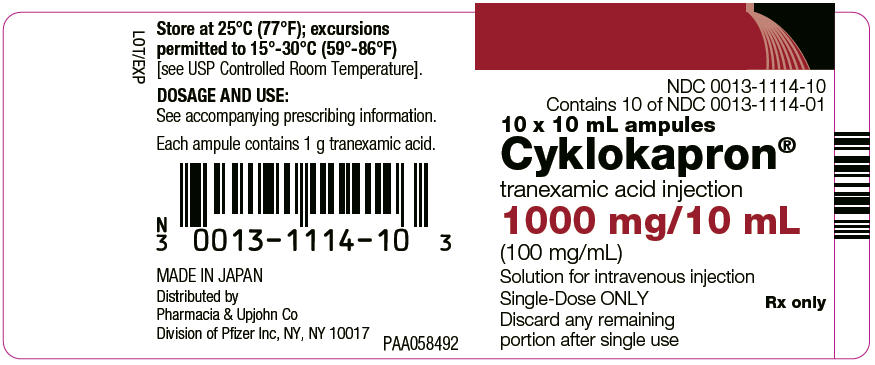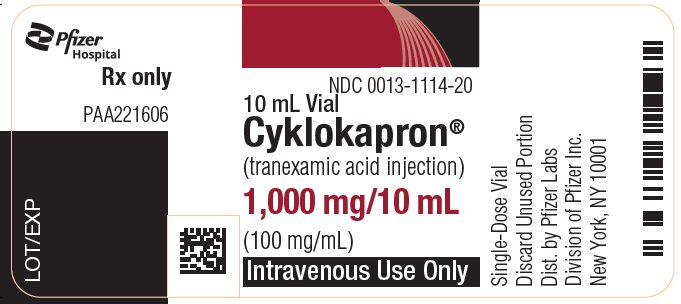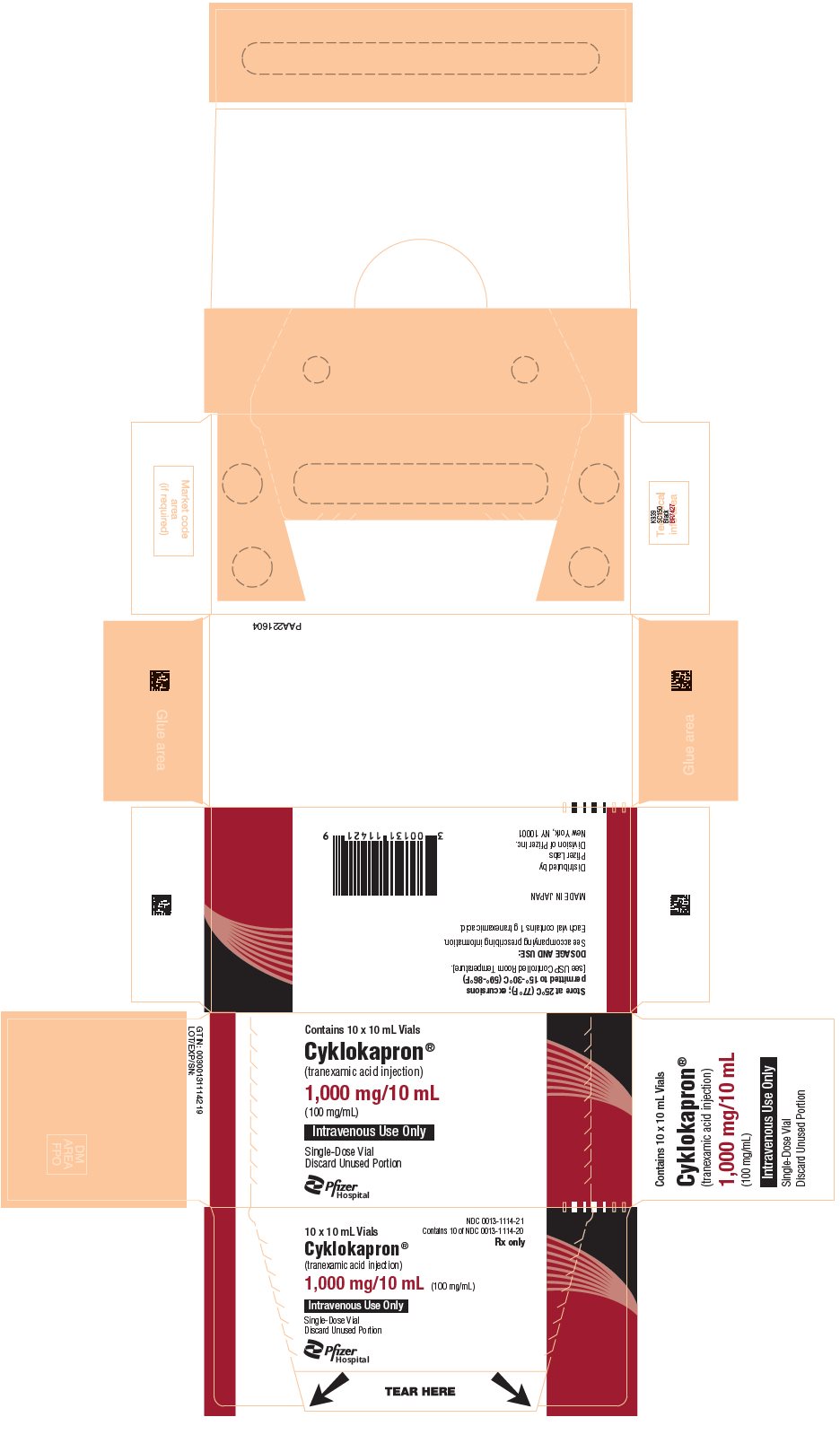 DRUG LABEL: Cyklokapron
NDC: 0013-1114 | Form: INJECTION, SOLUTION
Manufacturer: Pfizer Laboratories Div Pfizer Inc
Category: prescription | Type: HUMAN PRESCRIPTION DRUG LABEL
Date: 20250903

ACTIVE INGREDIENTS: TRANEXAMIC ACID 100 mg/1 mL
INACTIVE INGREDIENTS: WATER

HIGHLIGHTS OF PRESCRIBING INFORMATION

These highlights do not include all the information needed to use CYKLOKAPRON safely and effectively. See full prescribing information for CYKLOKAPRON.
CYKLOKAPRON® (tranexamic acid) injection, for intravenous use
Initial U.S. Approval: 1986

RECENT MAJOR CHANGES

Boxed Warning | 08/2025
Dosage and Administration (2) | 08/2025
Contraindication (4) | 08/2025
Warnings and Precautions (5) | 08/2025

WARNING: RISK OF MEDICATION ERRORS DUE TO INCORRECT ROUTE OF ADMINISTRATION

See full prescribing information for complete boxed warning.

CYKLOKAPRON is for intravenous use only. Serious, including fatal, adverse reactions including seizures and cardiac arrythmias have occurred when CYKLOKAPRON was inadvertently administered intrathecally via the neuraxial route. (5.1)

1 INDICATIONS AND USAGE

CYKLOKAPRON is an antifibrinolytic indicated in patients with hemophilia for short-term use (2 to 8 days) to reduce or prevent hemorrhage and reduce the need for replacement therapy during and following tooth extraction. (1)

2 DOSAGE AND ADMINISTRATION

- Before Extraction: Administer 10 mg/kg actual body weight of CYKLOKAPRON intravenously with replacement therapy as a single‑dose. (2.1)
- After Extraction: Administer 10 mg/kg actual body weight of CYKLOKAPRON intravenously 3 to 4 times daily for 2 to 8 days. (2.1)
- Infuse undiluted solution no more than 1 mL/minute to avoid hypotension. (2.3)
- Reduce the dosage for patients with renal impairment. (2.2, 8.6)

3 DOSAGE FORMS AND STRENGTHS

- Injection: 1,000 mg/10 mL (100 mg/mL) in single-dose ampules (3)
- Injection: 1,000 mg/10 mL (100 mg/mL) in single-dose vials (3)

4 CONTRAINDICATIONS

- As a neuraxial (i.e., intrathecal, epidural) injection. (4)
- In patients with subarachnoid hemorrhage, due to risk of cerebral edema and cerebral infarction. (4)
- In patients with active intravascular clotting. (4)
- In patients with severe hypersensitivity reactions to tranexamic acid or any of the ingredients. (4)

5 WARNINGS AND PRECAUTIONS

- Risk of Thrombosis with Concomitant Use of Factor IX: Avoid concomitant use. (5.2)
- Seizures: Inadvertent injection into neuraxial system may result in seizures. (5.3)
- Hypersensitivity Reactions: In case of severe reaction, discontinue use and seek immediate medical attention. (5.4)
- Visual Disturbances: Visual or ocular adverse effects may occur. Discontinue use if visual or ocular symptoms occur. (5.5)
- Dizziness: Advise patients not to drive if dizziness occurs. (5.6)

6 ADVERSE REACTIONS

Most common adverse reactions are nausea, vomiting, diarrhea, allergic dermatitis, giddiness, hypotension, and thromboembolic events. (6)
To report SUSPECTED ADVERSE REACTIONS, contact Pfizer Inc. at 1-800-438-1985 or FDA at 1-800-FDA-1088 or www.fda.gov/medwatch.

7 DRUG INTERACTIONS

Prothrombotic Medical Products: Avoid concomitant use, can further increase the risk of thromboembolic adverse reactions associated with tranexamic acid. (5.2, 7.1, 8.3)

FULL PRESCRIBING INFORMATION

WARNING: RISK OF MEDICATION ERRORS DUE TO INCORRECT ROUTE OF ADMINISTRATION

CYKLOKAPRON is for intravenous use only. Serious, including fatal, adverse reactions including seizures and cardiac arrythmias have occurred when CYKLOKAPRON was inadvertently administered via the neuraxial route [see Warnings and Precautions (5.1)].

1 INDICATIONS AND USAGE

CYKLOKAPRON® is indicated in patients with hemophilia for short-term use (2 to 8 days) to reduce or prevent hemorrhage and reduce the need for replacement therapy during and following tooth extraction.

2 DOSAGE AND ADMINISTRATION

2.1 Recommended Dosage

The recommended dose of CYKLOKAPRON is 10 mg/kg actual body weight administered as a single intravenous dose immediately before tooth extractions. Following tooth extraction, CYKLOKAPRON may be administered at a dose of 10 mg/kg actual body weight intravenously 3 to 4 times daily for 2 to 8 days.

2.2 Recommended Dosage for Patients With Varying Degrees of Renal Impairment

For patients with moderate to severe impaired renal function, the following dosages are recommended:

Table 1. Recommended Dosage in Patients With Varying Degrees of Renal Impairment [Dose reduction is recommended for all doses, both before and after tooth extraction.]
Serum Creatinine (mg/dL) | CYKLOKAPRON Dosage
1.36 mg/dL to 2.83 mg/dL | 10 mg/kg intravenously twice daily
2.83 mg/dL to 5.66 mg/dL | 10 mg/kg intravenously daily
>5.66 mg/dL | 10 mg/kg intravenously every 48 hours or 5 mg/kg intravenously every 24 hours

2.3 Preparation and Administration

CYKLOKAPRON is for intravenous administration only.

CYKLOKAPRON can be administered undiluted or as a diluted solution.

- Use aseptic technique to prepare CYKLOKAPRON.
- Parenteral drug products should be inspected visually for particulate matter and discoloration prior to administration, whenever solution and container permit. CYKLOKAPRON is a clear and colorless solution. Discard the vial if particulate matter is observed.
- Calculate the dose (mg) based on the patient’s actual body weight and the total volume (mL) of CYKLOKAPRON solution required.

If diluting CYKLOKAPRON, follow the instructions below:

- From the diluent infusion bag, withdraw a volume equal to the volume of the CYKLOKAPRON solution required for the patient’s dose.
- Withdraw the required volume of CYKLOKAPRON solution from the vial and dilute with a compatible diluent (see below) to make a final concentration of 10 mg/mL or 20 mg/mL. Discard any unused portion left in the vial.
  - For intravenous infusion, CYKLOKAPRON Injection may be mixed with most solutions for infusion such as electrolyte solutions, carbohydrate solutions, amino acid solutions, and Dextran solutions.
  - Heparin may be added to CYKLOKAPRON Injection.
  - CYKLOKAPRON Injection should NOT be mixed with blood.
  - The drug is a synthetic amino acid and should NOT be mixed with solutions containing penicillin.
- Gently invert the infusion bag to mix the diluted solution. DO NOT SHAKE.
- If not used immediately, store the diluted CYKLOKAPRON infusion solution at room temperature 20ºC to 25°C (68ºF to 77°F) for up to 4 hours.

Administration

Infuse undiluted solution no more than 1 mL/minute to avoid hypotension [see Adverse Reactions (6.2)].

Administer the undiluted and diluted solutions intravenously according to Table 2.

Table 2. Administration Rates for Undiluted and Diluted Solutions
 | Undiluted solution | Diluted solution
Final concentration | 100 mg/mL | 10 mg/mL | 20 mg/mL
Administration rate | 0.5 mL/minute (no more than 1 mL/minute) | 5 mL/minute | 2.5 mL/minute

3 DOSAGE FORMS AND STRENGTHS

Injection: 1,000 mg/10 mL (100 mg/mL) clear and colorless solution in single-dose ampules

Injection: 1,000 mg/10 mL (100 mg/mL) clear and colorless solution in single-dose vials

4 CONTRAINDICATIONS

CYKLOKAPRON Injection is contraindicated:

- As a neuraxial (i.e., intrathecal, epidural) injection [see Warnings and Precautions (5.1)].
- In patients with subarachnoid hemorrhage. Anecdotal experience indicates that cerebral edema and cerebral infarction may be caused by CYKLOKAPRON in such patients.
- In patients with active intravascular clotting [see Warnings and Precautions (5.2)].
- In patients with hypersensitivity to tranexamic acid or any of the ingredients [see Warnings and Precautions (5.4)].

5 WARNINGS AND PRECAUTIONS

5.1 Risk of Medication Errors Due to Incorrect Route of Administration

CYKLOKAPRON is for intravenous use only. Serious, including fatal, adverse reactions including seizures and cardiac arrythmias have occurred when CYKLOKAPRON was inadvertently administered via the neuraxial route.

Confirm the correct route of administration for CYKLOKAPRON and avoid confusion with other injectable solutions that might be administered at the same time as CYKLOKAPRON. Clearly label syringes containing CYKLOKAPRON with the intravenous route of administration.

5.2 Thromboembolic Risk

CYKLOKAPRON is contraindicated in patients with active intravascular clotting.

Tranexamic acid is an antifibrinolytic and may increase the risk of thromboembolic events. Venous and arterial thrombosis or thromboembolism has been reported in patients treated with CYKLOKAPRON. Avoid concomitant use of CYKLOKAPRON and medical products that are pro-thrombotic, as the risk of thrombosis may be increased. These medications include but are not limited to, Factor IX Complex concentrates, Anti-inhibitor Coagulant concentrates, and hormonal contraceptives [see Drug Interactions (7.1), Use in Specific Populations (8.3)].

5.3 Seizures

CYKLOKAPRON may cause seizures, including focal and generalized seizures. The most common setting for tranexamic acid-induced seizures has been during cardiovascular surgery (a setting in which CYKLOKAPRON is not FDA‑approved and which uses doses of up to 10‑fold higher than the recommended human dose and in patients inadvertently given tranexamic acid via the neuraxial route). CYKLOKAPRON is contraindicated for neuraxial administration (i.e., epidural, intrathecal). Consider dose reduction during surgery and dose adjustments for patients with clinical conditions such as renal dysfunction. Closely monitor the patient during surgery. Consider electroencephalogram (EEG) monitoring for patients with history of seizures or who experience myoclonic movements, twitching, or show evidence of focal seizures. Discontinue CYKLOKAPRON if seizures occur.

5.4 Hypersensitivity Reactions

Cases of hypersensitivity reactions, including anaphylactic reactions, have occurred with use of intravenous tranexamic acid. Discontinue treatment with CYKLOKAPRON if serious reaction occurs, provide appropriate medical management, and do not restart treatment. CYKLOKAPRON is contraindicated in patients with a history of hypersensitivity to tranexamic acid.

5.5 Visual Disturbances

Although not seen in humans, focal areas of retinal degeneration have been observed in cats and dogs following oral or intravenous tranexamic acid at doses between 250 to 1600 mg/kg/day (1.6 to 22 times the recommended usual human dose based on body surface area) from 6 days to 1 year. No retinal changes have been observed in eye examinations of patients treated with tranexamic acid for up to 8 years. Patients expected to be treated for greater than 3 months may consider ophthalmic monitoring including visual acuity and optical coherence tomography at regular intervals.

Discontinue CYKLOKAPRON if changes in ophthalmological examination occurs.

5.6 Dizziness

CYKLOKAPRON may cause dizziness. Concomitant use of other drugs that may also cause dizziness may worsen this effect. Advise patients to avoid driving or using machines until they know how CYKLOKAPRON affects them.

6 ADVERSE REACTIONS

The following clinically significant adverse reactions are described elsewhere in the labeling:

- Risk of Medication Errors Due to Incorrect Route of Administration [see Warnings and Precautions (5.1)]
- Thromboembolic Risk [see Warnings and Precautions (5.2)]
- Seizures [see Warnings and Precautions (5.3)]
- Hypersensitivity Reactions [see Warnings and Precautions (5.4)]
- Visual Disturbances [see Warnings and Precautions (5.5)]
- Dizziness [see Warnings and Precautions (5.6)]

6.2 Postmarketing Experience

The following adverse reactions have been identified during postapproval use of tranexamic acid. Because these reactions are reported voluntarily from a population of uncertain size, it is not always possible to reliably estimate their frequency or establish a causal relationship to drug exposure.

Gastrointestinal disturbances (nausea, vomiting, diarrhea) may occur and may resolve with dose-reduction. Allergic dermatitis and giddiness have been reported. Hypotension has been reported when intravenous injection is too rapid.

Thromboembolic events (e.g., deep vein thrombosis, pulmonary embolism, cerebral thrombosis, acute renal cortical necrosis, and central retinal artery, vein obstruction and cases associated with concomitant use of combination hormonal contraceptives) have been rarely reported in patients receiving tranexamic acid for indications other than hemorrhage prevention in patients with hemophilia. Convulsion, chromatopsia, and visual impairment have also been reported.

Anaphylaxis or anaphylactoid reactions have been reported that are suggestive of a causal relationship.

7 DRUG INTERACTIONS

7.1 Prothrombotic Medical Products

Avoid concomitant use of CYKLOKAPRON with medical products that are prothrombotic because concomitant use can further increase the risk of thromboembolic adverse reactions associated with tranexamic acid [see Warnings and Precautions (5.2), Use in Specific Populations (8.3)].

8 USE IN SPECIFIC POPULATIONS

8.1 Pregnancy

Risk Summary

Available data from published studies, case series and case reports with tranexamic acid use in pregnant women in the second and third trimester and at the time of delivery have not clarified whether there is a drug-associated risk of miscarriage or adverse maternal or fetal outcomes. There are 2 (0.02%) infant cases with structural abnormalities that resulted in death when tranexamic acid was used during conception or the first trimester of pregnancy; however, due to other confounding factors the risk of major birth defects with use of tranexamic acid during pregnancy is not clear. Tranexamic acid is known to pass the placenta and appears in cord blood at concentrations approximately equal to maternal concentration (see Data).

Reproduction studies performed in mice, rats, and rabbits have not revealed any adverse effects on the fetus due to tranexamic acid administered during organogenesis. Doses examined were multiples of up to 3 times (mouse), 6 times (rat), and 3 times (rabbit) the maximum human dose based on body surface area in the mouse, rat, and rabbit, respectively (see Data).

The estimated background risk for major birth defects and miscarriage for the indicated population is unknown. All pregnancies have a background risk of birth defect, loss, or other adverse outcomes. In the U.S. general population, the estimated background risk of major birth defects and miscarriage in the clinically recognized pregnancies is 2–4% and 15–20%, respectively.

It is not known whether tranexamic acid use in pregnant women may cause a drug-associated risk of miscarriage or adverse maternal or fetal outcomes. For decisions regarding the use of CYKLOKAPRON during pregnancy, the potential risk of CYKLOKAPRON administration on the fetus should always be considered along with the mother's clinical need for CYKLOKAPRON; an accurate risk-benefit evaluation should drive the treating physician's decision.

Data

Human Data

Tranexamic acid passes through the placenta. The concentration in cord blood after an intravenous injection of 10 mg/kg to pregnant women is about 30 mg/L, as high as in the maternal blood.

There were 13 clinical studies that described fetal and/or neonatal functional issues such as low Apgar score, neonatal sepsis, cephalohematoma and 9 clinical studies that discussed alterations to growth including low birth weight and preterm birth at 22–36 weeks of gestation in fetuses and infants exposed to tranexamic acid in-utero.

Animal Data

In embryo-fetal development studies, tranexamic acid was administered to pregnant mice from Gestation Day (GD) 6 through GD 12 and rats from GD 9 through GD 14 at daily doses of 0.3 or 1.5 g/kg. There was no evidence of adverse developmental outcomes in mice and rats at multiple of 3 and 6 times the maximum recommended human dose based on body surface area in the mouse and rat, respectively.

In rabbits, tranexamic acid was administered intravenously at doses of 50, 100, or 200 mg/kg/day or orally at doses of 100, 200, or 400 mg/kg/day from GD 6 through GD 18. There was no evidence of adverse developmental outcomes at dose multiples of 2 or 3 times, respectively, the maximum recommended human dose based on body surface area. Intravenous doses of 200 mg/kg/day showed slightly retarded weight gain in pregnant rabbits.

8.2 Lactation

Risk Summary

Published literature reports the presence of tranexamic acid in human milk. There are no data on the effects of tranexamic acid on the breastfed child or the effects on milk production. The developmental and health benefits of breastfeeding should be considered along with the mother's clinical need for CYKLOKAPRON and any potential adverse effects on the breastfed child from CYKLOKAPRON or from the underlying maternal condition.

8.3 Females and Males of Reproductive Potential

Contraception

Concomitant use of CYKLOKAPRON, which is an antifibrinolytic, with hormonal contraceptives may increase the risk for thromboembolic adverse reactions. Advise patients to use an effective alternative (nonhormonal) contraceptive method [see Warnings and Precautions (5.2), Drug Interactions (7.1)].

8.4 Pediatric Use

There are limited data concerning the use of CYKLOKAPRON in pediatric patients with hemophilia who are undergoing tooth extraction. The limited data suggest that there are no significant pharmacokinetic differences between adults and pediatric patients.

8.5 Geriatric Use

Clinical studies of CYKLOKAPRON did not include sufficient numbers of subjects aged 65 and over to determine whether they respond differently from younger subjects. Other reported clinical experience has not identified differences in responses between the elderly and younger patients.

This drug is known to be substantially excreted by the kidney, and the risk of toxic reactions to this drug may be greater in patients with impaired renal function. Because elderly patients are more likely to have decreased renal function, care should be taken in dose selection, and it may be useful to monitor renal function [see Dosage and Administration (2.2), Clinical Pharmacology (12.3)].

8.6 Renal Impairment

Reduce the dosage of CYKLOKAPRON in patients with renal impairment, based on the patient's serum creatinine [see Dosage and Administration (2.2), Clinical Pharmacology (12.3)].

10 OVERDOSAGE

Cases of overdosage of CYKLOKAPRON have been reported. Based on these reports, symptoms of overdosage may be gastrointestinal, e.g., nausea, vomiting, diarrhea; hypotensive, e.g., orthostatic symptoms; thromboembolic, e.g., arterial, venous, embolic; neurologic, e.g., visual impairment, convulsions, headache, mental status changes; myoclonus; and rash.

11 DESCRIPTION

Tranexamic acid is trans-4-(aminomethyl)cyclohexanecarboxylic acid, an antifibrinolytic agent. Tranexamic acid is a white crystalline powder. The structural formula is

Empirical Formula: C8H15NO2 Molecular Weight: 157.2

Each mL of the sterile solution for intravenous injection contains 100 mg tranexamic acid and Water for Injection to 1 mL. The aqueous solution for injection has a pH of 6.5 to 8.0.

12 CLINICAL PHARMACOLOGY

12.1 Mechanism of Action

Tranexamic acid is a synthetic lysine amino acid derivative, which diminishes the dissolution of hemostatic fibrin by plasmin. In the presence of tranexamic acid, the lysine receptor binding sites of plasmin for fibrin are occupied, preventing binding to fibrin monomers, thus preserving and stabilizing fibrin's matrix structure.

The antifibrinolytic effects of tranexamic acid are mediated by reversible interactions at multiple binding sites within plasminogen. Native human plasminogen contains 4 to 5 lysine binding sites with low affinity for tranexamic acid (Kd = 750 μmol/L) and 1 with high affinity (Kd = 1.1 μmol/L). The high affinity lysine site of plasminogen is involved in its binding to fibrin. Saturation of the high affinity binding site with tranexamic acid displaces plasminogen from the surface of fibrin. Although plasmin may be formed by conformational changes in plasminogen, binding to and dissolution of the fibrin matrix is inhibited.

12.2 Pharmacodynamics

Tranexamic acid, in concentrations of 1 mg/mL and 10 mg/mL prolongs the thrombin time. An antifibrinolytic concentration of tranexamic acid remains in different tissues for about 17 hours, and in the serum, up to 7 or 8 hours.

Tranexamic acid in concentrations up to 10 mg/mL blood has no influence on the platelet count, the coagulation time or various coagulation factors in whole blood or citrated blood from healthy subjects.

12.3 Pharmacokinetics

Distribution

The initial volume of distribution is about 9 to 12 liters. The plasma protein binding of tranexamic acid is about 3% at therapeutic plasma levels and seems to be fully accounted for by its binding to plasminogen. Tranexamic acid does not bind to serum albumin.

Elimination

After an intravenous dose of 1 g, the plasma concentration time curve shows a triexponential decay with a half-life of about 2 hours for the terminal elimination phase.

Excretion

Urinary excretion is the main route of elimination via glomerular filtration. Overall renal clearance is equal to overall plasma clearance (110 to 116 mL/min), and more than 95% of the dose is excreted in the urine as unchanged drug. Excretion of tranexamic acid is about 90% at 24 hours after intravenous administration of 10 mg/kg body weight.

Specific Populations

Patients with Renal Impairment

The blood levels of tranexamic acid are increased in patients with renal insufficiency. Urinary excretion following a single intravenous injection of tranexamic acid declines as renal function decreases. Following a single 10 mg/kg intravenous injection of tranexamic acid, the 24-hour urinary fractions of tranexamic acid with serum creatinine concentrations 1.4 – 2.8, 2.8 – 5.7, and greater than 5.7 mg/dL were 51, 39, and 19%, respectively. The 24-hour tranexamic acid plasma concentrations for these patients demonstrated a direct relationship to the degree of renal impairment. Therefore, dose adjustment is needed in patients with renal impairment [see Dosage and Administration (2.2), Use in Specific Populations (8.6)].

Drug Interaction Studies

No studies of interactions between CYKLOKAPRON and other drugs have been conducted.

13 NONCLINICAL TOXICOLOGY

13.1 Carcinogenesis, Mutagenesis, Impairment of Fertility

Tranexamic acid was not carcinogenic in a 2-year study in rats and mice at oral doses up to 3 and 5.3 g/kg/day, which are approximately 12 and 11 times the maximum recommended human dose based on body surface area, respectively.

Tranexamic acid was not genotoxic in the reverse mutation bacterial (Ames) test, and in vitro and in vivo cytogenetic test.

In a fertility and early embryonic development study, tranexamic acid was administered to male rats as 0.3% and 1% of drug in diet (average doses of 222 and 856 mg/kg/day) or to female rats at dose levels of 0.3% and 1.2% of drug in diet. Tranexamic acid had no effect on fertility or reproductive function of male or female rats at dose multiples of 4 or 5 times the maximum recommended human dose based on body surface area, respectively.

13.2 Animal Toxicology and/or Pharmacology

Nonclinical studies have shown a retinal toxicity associated with tranexamic acid. Toxicity is characterized by retinal atrophy commencing with changes to the retinal pigmented epithelium and progressing to retinal detachment in cats. The toxicity appears to be dose related, and changes are partially reversible at lower doses. Effects were observed in dogs at oral doses of 800 mg/kg/day and higher (multiple of 11 times the maximum human dose based on body surface area), and in cats at 250 mg/kg/day for 14 days (multiple of 1.6 times the maximum human dose based on body surface area). Some fully reversible changes in pigmentation were observed in cats at doses of 125 mg/kg/day (multiple of 0.8 times the maximum human dose based on body surface area). Studies suggest that the underlying mechanism may be related to a transient retinal ischemia at high exposures, linked to the known sympathomimetic effect of high plasma exposures of tranexamic acid.

16 HOW SUPPLIED/STORAGE AND HANDLING

CYKLOKAPRON Injection is a clear and colorless solution supplied in the following presentations:

CYKLOKAPRON Injection 1,000 mg/10 mL (100 mg/mL)
NDC 0013-1114-10 | 10 × 10 mL single-dose ampules
NDC 0013-1114-15 | 1 × 10 mL single-dose ampule
CYKLOKAPRON Injection 1,000 mg/10 mL (100 mg/mL)
NDC 0013-1114-21 | 10 × 10 mL single-dose vials

Store at 20ºC to 25°C (68ºF to 77°F); excursions permitted to 15°C to 30°C (59°F to 86°F) [see USP Controlled Room Temperature].

17 PATIENT COUNSELING INFORMATION

Thromboembolic Risk

Inform patients that CYKLOKAPRON may increase the risk of venous and arterial thrombosis or thromboembolism and to contact their healthcare provider for any signs or symptoms suggestive of thromboembolism.

Advise patients using hormonal contraception that combined use with CYKLOKAPRON may increase the risk for thromboembolic adverse reactions and to use effective alternative (nonhormonal) contraception during therapy with CYKLOKAPRON [see Warnings and Precautions (5.2), Drug Interactions (7.1), Use in Specific Populations (8.3)].

Seizures

Inform patients that CYKLOKAPRON may cause seizures and to contact their healthcare provider for any signs or symptoms suggestive of seizures [see Warnings and Precautions (5.3)].

Hypersensitivity Reactions

Inform patients that CYKLOKAPRON may cause hypersensitivity reactions and to contact their healthcare provider for any signs or symptoms of hypersensitivity reactions [see Warnings and Precautions (5.4)].

Visual Disturbances

Inform patients that CYKLOKAPRON can cause visual disturbance and that they should report any eye symptoms or change in their vision to their healthcare provider and to follow-up with an ophthalmologist for a complete ophthalmologic evaluation, including dilated retinal examination of the retina [see Warnings and Precautions (5.5)].

Risk of Driving and Operating Machinery

Inform patients that CYKLOKAPRON may cause dizziness, and that the patient should be cautioned about driving, operating machinery, or performing hazardous tasks while taking CYKLOKAPRON [see Warnings and Precautions (5.6)].

This product's labeling may have been updated. For the most recent prescribing information, please visit www.pfizer.com.

LAB-0258-19.0

PRINCIPAL DISPLAY PANEL - 10 mL Ampule Label

Pfizer

NDC 0013-1114-01

10 mL ampule

Cyklokapron®
(tranexamic acid injection)

1,000 mg/10 mL

(100 mg/mL)
Intravenous Use Only
Single-Dose Ampule
Discard Unused Portion

PAA221603

PRINCIPAL DISPLAY PANEL - 10 mL Ampule Carton - NDC 0013-1114-01

NDC 0013-1114-01

Contains 1 Ampule 10 mL
Cyklokapron®
tranexamic acid injection

1000 mg/10 mL
(100 mg/mL)

Solution for intravenous injection

Single-Dose ONLY
Discard any remaining portion
after single use

Rx only

Pfizer Injectables

PRINCIPAL DISPLAY PANEL - 10 mL Ampule Carton - NDC 0013-1114-15

NDC 0013-1114-15

Contains 1 Ampule 10 mL

Cyklokapron®
(tranexamic acid injection)

1,000 mg/10 mL
(100 mg/mL)

Intravenous Use Only

Single-Dose Ampule
Discard Unused Portion

Rx only

Pfizer
Hospital

PRINCIPAL DISPLAY PANEL - 10 x 10 mL Ampule Box Label

NDC 0013-1114-10
Contains 10 of NDC 0013-1114-01
10 x 10 mL ampules
Cyklokapron®
tranexamic acid injection
1000 mg/10 mL
(100 mg/mL)
Solution for intravenous injection
Single-Dose ONLY
Discard any remaining
portion after single use

Rx only

PRINCIPAL DISPLAY PANEL - 10 mL Vial Label

NDC 0013-1114-20

10 mL Vial

Cyklokapron®
(tranexamic acid injection)

1,000 mg/10 mL

(100 mg/mL)

Intravenous Use Only

PRINCIPAL DISPLAY PANEL - 10 mL Vial Box

NDC 0013-1114-21
Contains 10 of NDC 0013-1114-20
Rx only

10 x 10 mL Vials

Cyklokapron®
(tranexamic acid injection)

1,000 mg/10 mL (100 mg/mL)

Intravenous Use Only

Single-Dose Vial
Discard Unused Portion

Pfizer
Hospital

TEAR HERE